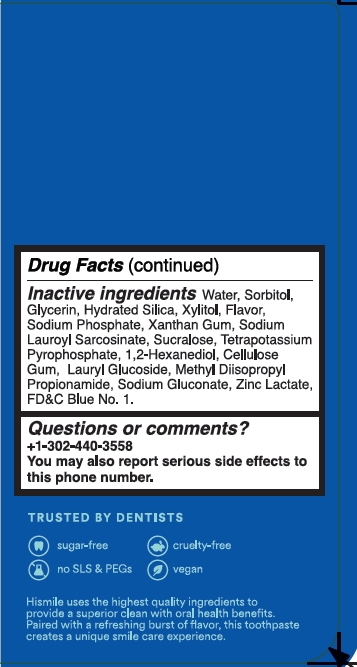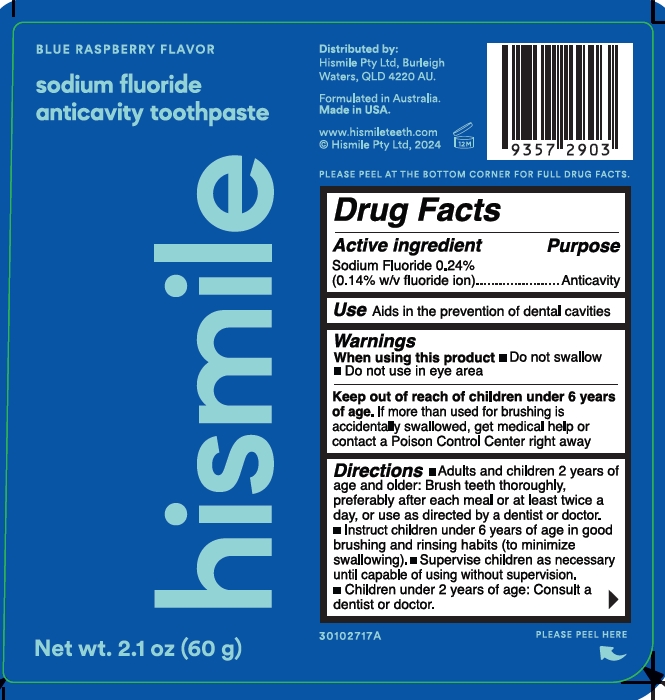 DRUG LABEL: HISMILE
NDC: 83013-326 | Form: GEL
Manufacturer: HISMILE PTY LTD
Category: otc | Type: HUMAN OTC DRUG LABEL
Date: 20260115

ACTIVE INGREDIENTS: SODIUM FLUORIDE 0.243 g/100 g
INACTIVE INGREDIENTS: XYLITOL; HYDRATED SILICA; SODIUM LAUROYL SARCOSINATE; GLYCERIN; 1,2-HEXANEDIOL; CARBOXYMETHYLCELLULOSE SODIUM, UNSPECIFIED FORM; WATER; SORBITOL; SODIUM PHOSPHATE; XANTHAN GUM; POTASSIUM PYROPHOSPHATE; SUCRALOSE; LAURYL GLUCOSIDE; SODIUM GLUCONATE; ZINC LACTATE; METHYL DIISOPROPYL PROPIONAMIDE; FD&C BLUE NO. 1

Blue Raspberry Sodium Fluoride Anticavity Toothpaste

Active ingredient

Sodium Fluoride 0.243%

(0.14 w/v fluoride ion)

Purpose

Anticavity

Use

Aids in the prevention of dental cavities

Warnings

When using this product

- Do not swallow
- Do not use in eye area

Keep out of reach of children under 6 years of age

If more than used for brushing is accidentally swallowed, get medical help or contact a Poison Control Center right away.

Directions

- Adults and children 2 years of age and older: Brush teeth thoroughly, preferably after each meal or at least twice a day, or use as directed by a dentist or doctor.
- Instruct children under 6 years of age in good brushing and rinsing habtis (to minimize swallowing).
- Supervise children as necessary until capable of using without supervision.
- Children under 2 years of age: Consult a dentist or doctor.

Inactive ingredients

Water

Sorbitol

Glycerin

Hydrated Silica

Xylitol

Sodium Phosphate

Xanthan Gum

Sodium Lauroyl Sarcosinate

Tetrapotassium Pyrophosphate

1,2-Hexanediol

Cellulose Gum

Sucralose

Lauryl Glucoside

Methyl Diisopropyl Propionamide

Sodium Gluconate

Zinc Lactate

FD&C Blue No. 1.